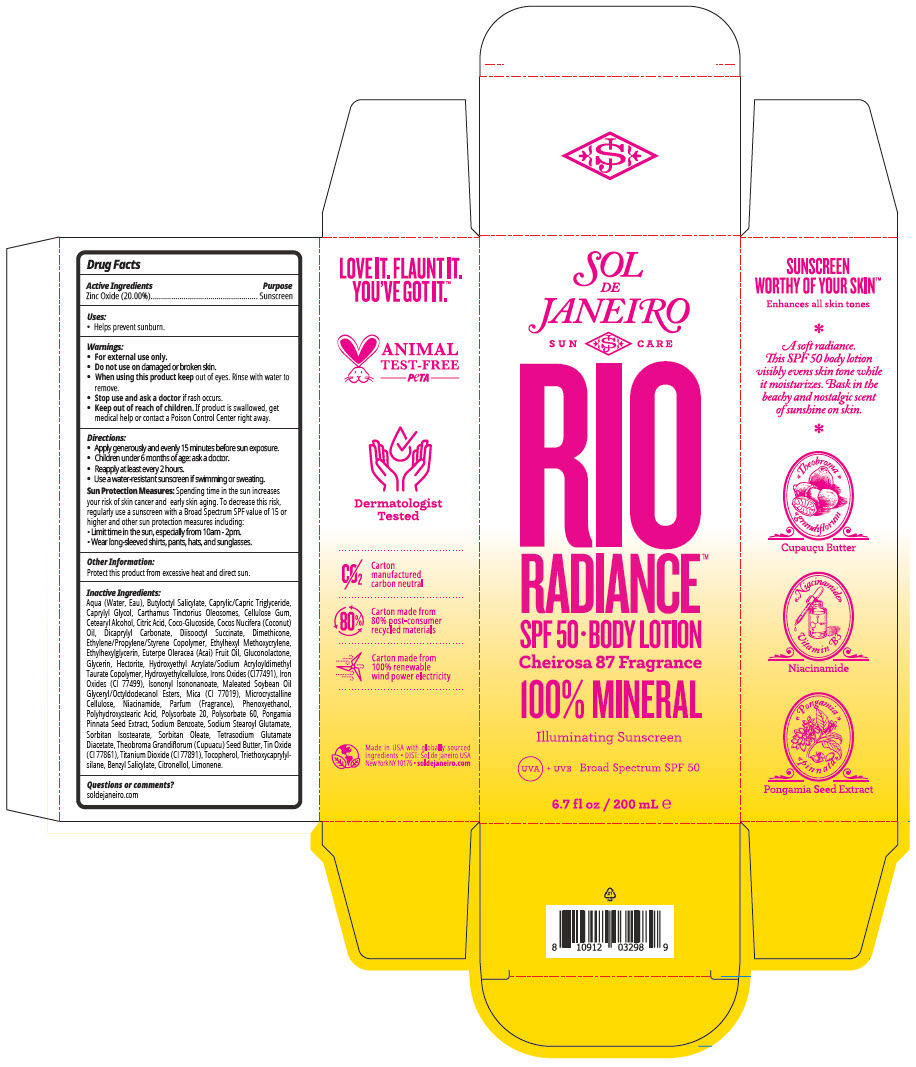 DRUG LABEL: Sol de Janiero Rio Radiance SPF 50 Body
NDC: 66163-4838 | Form: LOTION
Manufacturer: Cosmetic Solutions LLC
Category: otc | Type: HUMAN OTC DRUG LABEL
Date: 20260202

ACTIVE INGREDIENTS: Zinc Oxide 20 g/100 mL
INACTIVE INGREDIENTS: WATER; BUTYLOCTYL SALICYLATE; MEDIUM-CHAIN TRIGLYCERIDES; CAPRYLYL GLYCOL; CARTHAMUS TINCTORIUS SEED OLEOSOMES; CARBOXYMETHYLCELLULOSE SODIUM, UNSPECIFIED; CETOSTEARYL ALCOHOL; CITRIC ACID MONOHYDRATE; COCO-GLUCOSIDE; COCONUT OIL; DICAPRYLYL CARBONATE; DIMETHICONE, UNSPECIFIED; ETHYLHEXYL METHOXYCRYLENE; ETHYLHEXYLGLYCERIN; ACAI OIL; GLUCONOLACTONE; GLYCERIN; HECTORITE; HYDROXYETHYL CELLULOSE, UNSPECIFIED; FERRIC OXIDE RED; FERROSOFERRIC OXIDE; ISONONYL ISONONANOATE; MICA; MICROCRYSTALLINE CELLULOSE; NIACINAMIDE; PHENOXYETHANOL; POLYSORBATE 20; POLYSORBATE 60; PONGAMIA PINNATA SEED; SODIUM BENZOATE; SODIUM STEAROYL GLUTAMATE; SORBITAN ISOSTEARATE; SORBITAN MONOOLEATE; TETRASODIUM GLUTAMATE DIACETATE; STANNIC OXIDE; TITANIUM DIOXIDE; TOCOPHEROL; TRIETHOXYCAPRYLYLSILANE; BENZYL SALICYLATE; .BETA.-CITRONELLOL, (R)-; LIMONENE, (+)-

Sol de Janiero Rio Radiance™ SPF 50 Body Lotion

Drug Facts

Active Ingredients

Zinc Oxide (20.00%)

Purpose

Sunscreen

Uses

- Helps prevent sunburn.

Warnings

- For external use only.
- Do not use on damaged or broken skin.
- When using this product keep out of eyes. Rinse with water to remove.
- Stop use and ask a doctor if rash occurs.

- Keep out of reach of children. If product is swallowed, get medical help or contact a Poison Control Center right away.

Directions

- Apply generously and evenly 15 minutes before sun exposure.
- Children under 6 months of age: ask a doctor.
- Reapply at least every 2 hours.
- Use a water-resistant sunscreen if swimming or sweating.

Sun Protection Measures

Spending time in the sun increases your risk of skin cancer and early skin aging. To decrease this risk, regularly use a sunscreen with a Broad Spectrum SPF value of 15 or higher and other sun protection measures including:

- Limit time in the sun, especially from 10am - 2pm.
- Wear long-sleeved shirts, pants, hats, and sunglasses.

Other Information

Protect this product from excessive heat and direct sun.

Inactive Ingredients

Aqua (Water, Eau), Butyloctyl Salicylate, Caprylic/Capric Triglyceride, Caprylyl Glycol, Carthamus Tinctorius Oleosomes, Cellulose Gum, Cetearyl Alcohol, Citric Acid, Coco-Glucoside, Cocos Nucifera (Coconut) Oil, Dicaprylyl Carbonate, Diisooctyl Succinate, Dimethicone, Ethylene/Propylene/Styrene Copolymer, Ethylhexyl Methoxycrylene, Ethylhexylglycerin, Euterpe Oleracea (Acai) Fruit Oil, Gluconolactone, Glycerin, Hectorite, Hydroxyethyl Acrylate/Sodium Acryloyldimethyl Taurate Copolymer, Hydroxyethylcellulose, Irons Oxides (CI77491), Iron Oxides (CI 77499), Isononyl Isononanoate, Maleated Soybean Oil Glyceryl/Octyldodecanol Esters, Mica (CI 77019), Microcrystalline Cellulose, Niacinamide, Parfum (Fragrance), Phenoxyethanol, Polyhydroxystearic Acid, Polysorbate 20, Polysorbate 60, Pongamia Pinnata Seed Extract, Sodium Benzoate, Sodium Stearoyl Glutamate, Sorbitan Isostearate, Sorbitan Oleate, Tetrasodium Glutamate Diacetate, Theobroma Grandiflorum (Cupuacu) Seed Butter, Tin Oxide (CI 77861), Titanium Dioxide (CI 77891), Tocopherol, Triethoxycaprylylsilane, Benzyl Salicylate, Citronellol, Limonene.

Questions or comments?

soldejaneiro.com

PRINCIPAL DISPLAY PANEL - 200 mL Bottle Carton

SOL
DE
JANEIRO

SUN
CARE

RIO
RADIANCE™
SPF 50 • BODY LOTION

Cheirosa 87 Fragrance

100% MINERAL

Illuminating Sunscreen

UVA + UVB Broad Sprectrum SPF 50

6.7 fl oz / 200 mL ℮